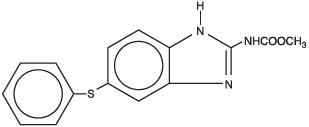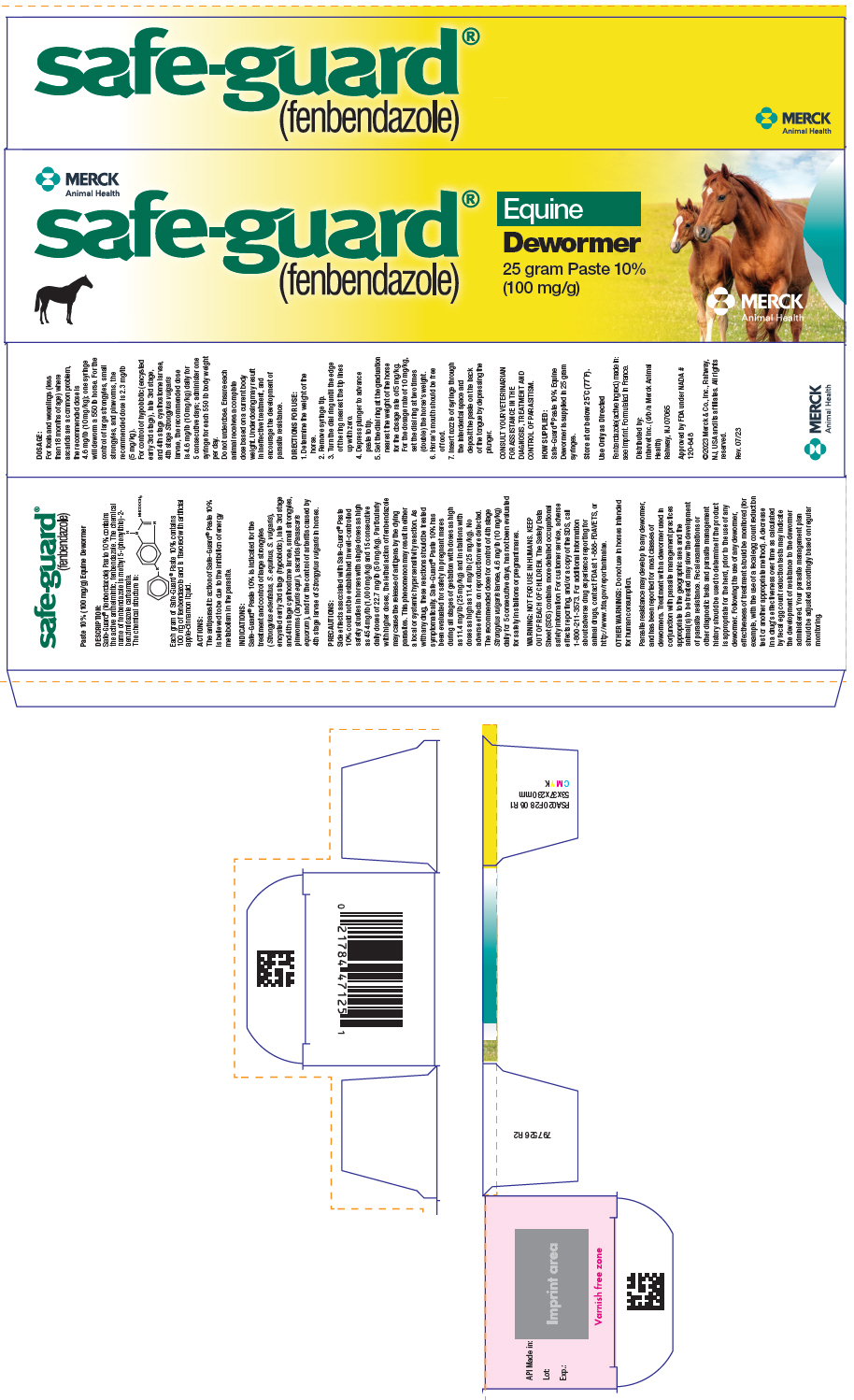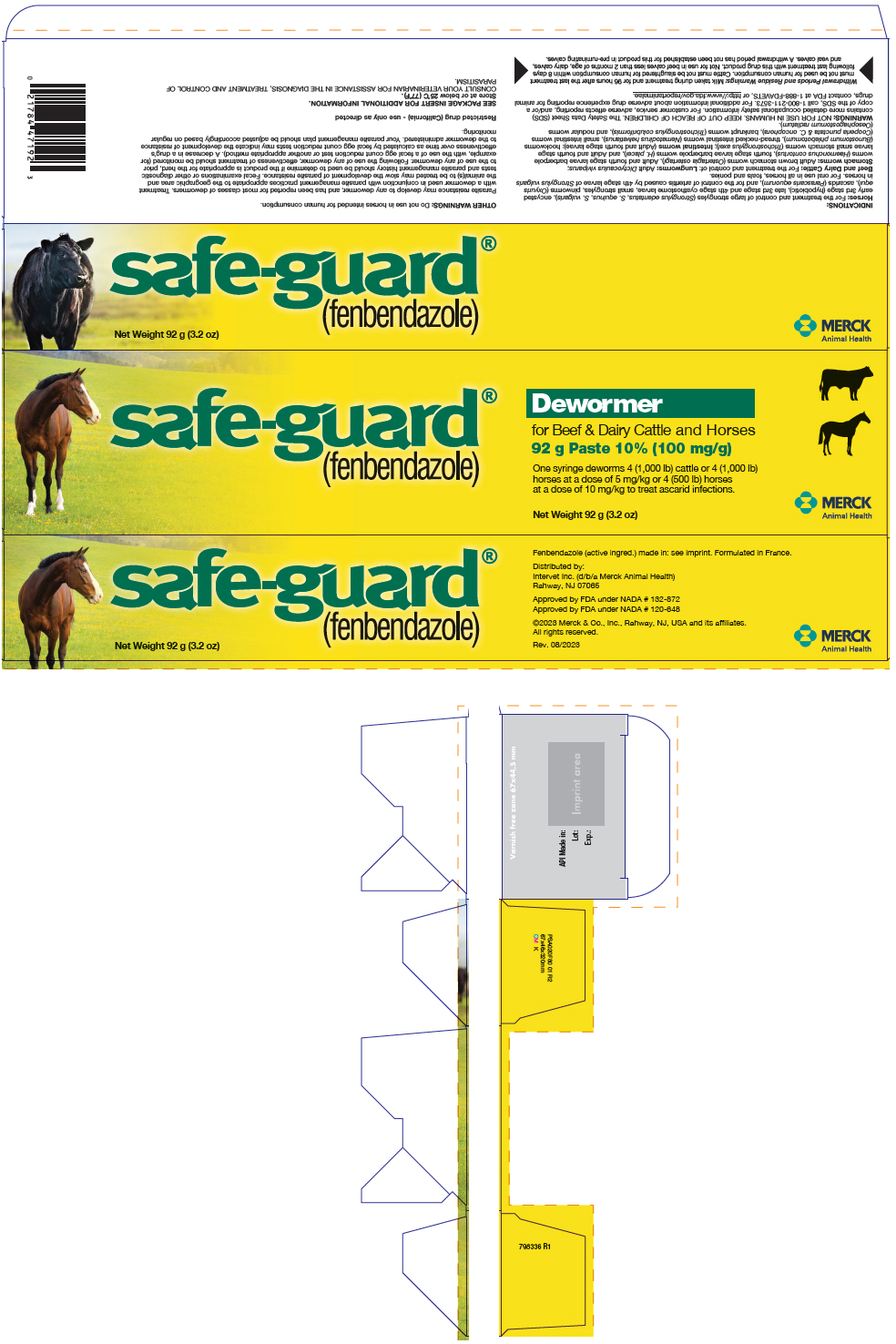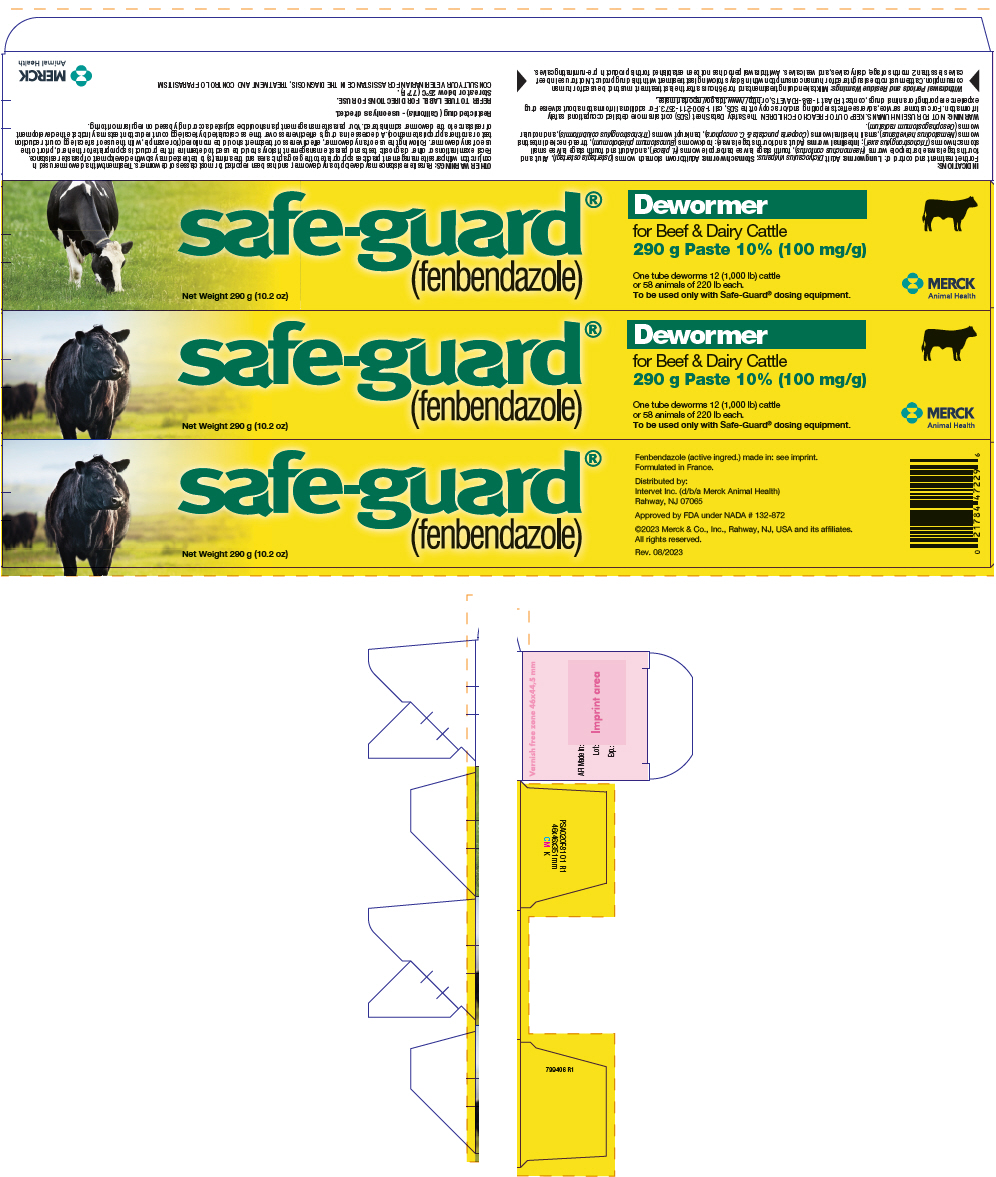 DRUG LABEL: Safe-guard
NDC: 57926-083 | Form: PASTE
Manufacturer: Merck Sharp & Dohme Corp.
Category: animal | Type: OTC ANIMAL DRUG LABEL
Date: 20241119

ACTIVE INGREDIENTS: FENBENDAZOLE 100 mg/1 g

safe-guard®
(fenbendazole)

Paste 10% (100 mg/g)
HORSE AND CATTLE DEWORMER

797851 R1

DESCRIPTION:

Safe-Guard® (fenbendazole) Paste 10% contains the active anthelmintic, fenbendazole. The chemical name of fenbendazole is methyl 5-(phenyl-thio)-2-benzimidazole carbamate.

The CAS Registry Number is 43210-67-9.

The chemical structure is:

Each gram of Safe-Guard® Paste 10% contains 100 mg of fenbendazole and is flavored with artificial apple-cinnamon liquid.

ACTIONS:

The antiparasitic action of Safe-Guard® Paste 10% is believed to be due to the inhibition of energy metabolism in the parasite.

INDICATIONS:

Horses: For the treatment and control of large strongyles (Strongylus edentatus, S. equinus, S. vulgaris), encysted early 3rd stage (hypobiotic), late 3rd stage and 4th stage cyathostome larvae, small strongyles, pinworms (Oxyuris equi), ascarids (Parascaris equorum), and for the control of arteritis caused by 4th stage larvae of Strongylus vulgaris in horses.

Beef and Dairy Cattle: For the treatment and control of: Lungworms: Adult Dictyocaulus viviparus; Stomach worms: Adult brown stomach worms (Ostertagia ostertagi), Adult and fourth stage larvae barberpole worms (Haemonchus contortus), fourth stage larvae barberpole worms (H. placei), and Adult and fourth stage larvae small stomach worms (Trichostrongylus axei); Intestinal worms (Adult and fourth stage larvae): hookworms (Bunostomum phlebotomum), thread-necked intestinal worms (Nematodirus helvetianus), small intestinal worms (Cooperia punctata & C. oncophora), bankrupt worms (Trichostrongylus colubriformis), and nodular worms (Oesophagostomum radiatum).

One syringe deworms 4 (1,000 lb) cattle or 4 (1,000 lb) horses at a dose of 5 mg/kg or 4 (500 lb) horses at a dose of 10 mg/kg to treat ascarid infections.

PRECAUTIONS:

Horses: Side effects associated with Safe-Guard® Paste 10% could not be established in well-controlled safety studies in horses with single doses as high as 454 mg/lb (1,000 mg/kg) and 15 consecutive daily doses of 22.7 mg/lb (50 mg/kg). At higher dose levels, the lethal action of fenbendazole may cause the release of antigens by the dying parasites. This phenomenon may result in either a local or systemic hypersensitivity reaction varying in severity from itching or a rash to increased respiration and collapse. A veterinarian should be consulted if this type of reaction is suspected.

Safe-Guard® Paste 10% has been evaluated for safety in pregnant mares during all stages of gestation with doses as high as 11.4 mg/lb (25 mg/kg) and in stallions with doses as high as 11.4 mg/lb (25 mg/kg). No adverse effects on reproduction were detected. The recommended dose for control of 4th stage Strongylus vulgaris larvae, 4.6 mg/lb (10 mg/kg) daily for 5 consecutive days, has not been evaluated for safety in stallions or pregnant mares.

DOSAGE:

Do not underdose. Ensure each animal receives a complete dose based on a current body weight. Underdosing may result in ineffective treatment, and encourage the development of parasite resistance.

Horses: Safe-Guard® Paste 10% is administered orally at a rate of 2.3 mg/lb (5 mg/kg) for the control of large strongyles, small strongyles, and pinworms. Each mark on the plunger rod corresponds to a dose of 2.3 mg/lb (5 mg/kg) for 250 lb body weight.

For foals and weanlings (less than 18 months of age) where ascarids are a common problem, the recommended dose of 4.6 mg/lb (10 mg/kg), or two marks, will deworm a 250 Ib horse.

For control of hypobiotic (encysted early 3rd stage), late 3rd stage, and 4th stage cyathostome larvae, as well as 4th stage Strongylus vulgaris larvae, the recommended dose is 4.6 mg/lb (10 mg/kg) daily for 5 consecutive days; administer two marks for each 250 Ib body weight per day.

Beef and Dairy Cattle: Safe-Guard® Paste 10% is administered orally at a rate of 2.3 mg/lb (5 mg/kg) or 11.5 g Safe-Guard® Paste for 500 Ib body weight (227 kg).

RESIDUE WARNING

Withdrawal Periods and Residue Warnings: Milk taken during treatment and for 96 hours after the last treatment must not be used for human consumption. Cattle must not be slaughtered for human consumption within 8 days following last treatment with this drug product. Not for use in beef calves less than 2 months of age, dairy calves, and veal calves. A withdrawal period has not been established for this product in pre-ruminating calves.

WARNINGS

WARNINGS: NOT FOR USE IN HUMANS. KEEP OUT OF REACH OF CHILDREN. The Safety Data Sheet (SDS) contains more detailed occupational safety information. For customer service, adverse effects reporting, and/or a copy of the SDS, call 1-800-211-3573. For additional information about adverse drug experience reporting for animal drugs, contact FDA at 1-888-FDAVETS, or http://www.fda.gov/reportanimalae.

OTHER WARNINGS: Do not use in horses intended for human consumption.

Parasite resistance may develop to any dewormer, and has been reported for most classes of dewormers. Treatment with a dewormer used in conjunction with parasite management practices appropriate to the geographic area and the animal(s) to be treated may slow the development of parasite resistance. Fecal examinations or other diagnostic tests and parasite management history should be used to determine if the product is appropriate for the herd, prior to the use of any dewormer. Following the use of any dewormer, effectiveness of treatment should be monitored (for example, with the use of a fecal egg count reduction test or another appropriate method). A decrease in a drug's effectiveness over time as calculated by fecal egg count reduction tests may indicate the development of resistance to the dewormer administered. Your parasite management plan should be adjusted accordingly based on regular monitoring.

DIRECTIONS FOR USE:

1. Determine the weight of the animal.
2. Remove syringe tip.
3. Turn the dial ring until the edge of the ring nearest the tip lines up with zero.
4. Fully depress plunger and discard expelled paste. Syringe is ready for dosing.
5. Each mark on the plunger rod corresponds to a dose of 2.3 mg/lb (5 mg/kg) for 250 lb body weight, or a dose of 4.6 mg/lb (10 mg/kg) for 125 lb body weight (the 10 mg/kg dose is for horses only).
  Dial the ring edge nearest the tip back by the calculated number of marks on the plunger rod corresponding to the animal's body weight.
  Examples:
  Body Weight | Number of marks for 2.3 mg/lb (5 mg/kg) dose for cattle or horses | Number of marks for 4.6 mg/lb (10 mg/kg) dose for horses only
  250 lb | 1 | 2
  500 lb | 2 | 4
  750 lb | 3 | 6
  1000 lb | 4 | 8
  1500 lb | 6 | 12
6. The animal's mouth should be free of food. Insert nozzle of syringe through the interdental space and deposit the paste on the back of the tongue by depressing the plunger.
7. Repeat steps 1, 5 and 6 for each additional animal.

HOW SUPPLIED:

Safe-Guard® Paste 10% Horse and Cattle Dewormer is supplied in 92 gram syringes.

STORAGE AND HANDLING

Store at or below 25°C (77°F).

CONSULT YOUR VETERINARIAN FOR ASSISTANCE IN THE DIAGNOSIS, TREATMENT AND CONTROL OF PARASITISM.

Formulated in France.
Distributed by:
Intervet Inc. (d/b/a Merck Animal Health)
Rahway, NJ 07065

Approved by FDA under NADA # 132-872
Approved by FDA under NADA # 120-648

©2023 Merck & Co., Inc., Rahway, NJ, USA and its affiliates. All rights reserved.

Rev. 08/23

MERCK
Animal Health

PRINCIPAL DISPLAY PANEL - 25 g Syringe Carton

MERCK
Animal Health

safe-guard®
(fenbendazole)

Equine
Dewormer

25 gram Paste 10%
(100 mg/g)

MERCK
Animal Health

PRINCIPAL DISPLAY PANEL - 92 g Syringe Carton

safe-guard®
(fenbendazole)

Dewormer

for Beef & Dairy Cattle and Horses
92 g Paste 10% (100 mg/g)

One syringe deworms 4 (1,000 lb) cattle or 4 (1,000 lb)
horses at a dose of 5 mg/kg or 4 (500 lb) horses
at a dose of 10 mg/kg to treat ascarid infections.

Net Weight 92 g (3.2 oz)

MERCK
Animal Health

PRINCIPAL DISPLAY PANEL - 290 g Syringe Carton

safe-guard®
(fenbendazole)

Dewormer

for Beef & Dairy Cattle
290 g Paste 10% (100 mg/g)

One tube deworms 12 (1,000 lb) cattle
or 58 animals of 220 lb each.
To be used only with Safe-Guard® dosing equipment.

Net Weight 290 g (10.2 oz)

MERCK
Animal Health